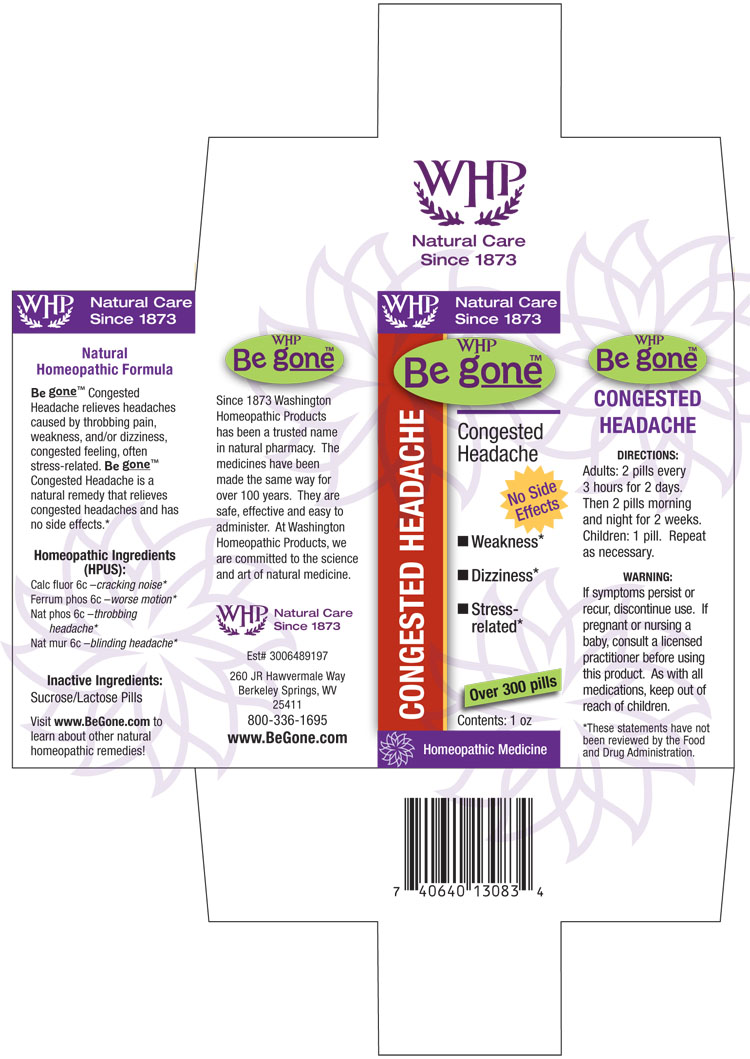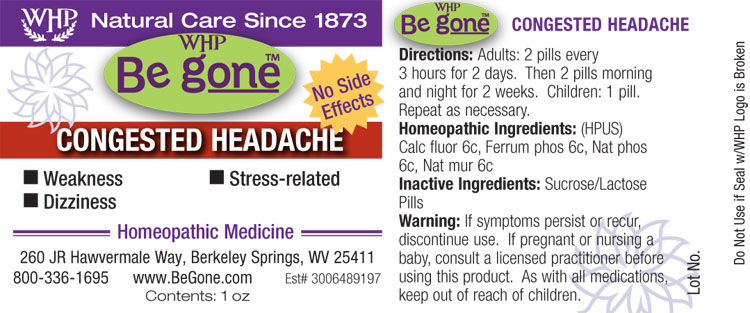 DRUG LABEL: WHP Be gone Congested Headache
NDC: 68428-747 | Form: PELLET
Manufacturer: Washington Homeopathic Products
Category: homeopathic | Type: HUMAN OTC DRUG LABEL
Date: 20140508

ACTIVE INGREDIENTS: CALCIUM FLUORIDE 6 [hp_C]/1 1; FERROSOFERRIC PHOSPHATE 6 [hp_C]/1 1; SODIUM PHOSPHATE, DIBASIC, HEPTAHYDRATE 6 [hp_C]/1 1; SODIUM CHLORIDE 6 [hp_C]/1 1
INACTIVE INGREDIENTS: SUCROSE; LACTOSE

DRUG FACTS

ACTIVE INGREDIENTS

CALC FLUOR

FERRUM PHOS

NAT PHOS

NAT MUR

USES

Relieves headaches caused by throbbing pain, weakness, and/or dizziness, congested feeling, often stress-related.

KEEP OUT OF REACH OF CHILDREN

As with all medications, keep out of reach of children.

INDICATIONS

Calc fluor 6c –cracking noise*

Ferrum phos 6c –worse motion*

Nat phos 6c –throbbing headache*

Nat mur 6c –blinding headache*

■ Weakness* ■ Dizziness* ■ Stress-related*

*These statements have not been reviewed by the Food and Drug Administration.

STOP USE AND ASK DOCTOR

If symptoms persist or recur, discontinue use. If pregnant or nursing a baby, consult a licensed practitioner before using this product.

DIRECTIONS

Adults: 2 pills every 3 hours for 2 days. Then 2 pills morning and night for 2 weeks.

Children: 1 pill.

Repeat as necessary.

INACTIVE INGREDIENTS

Sucrose/Lactose